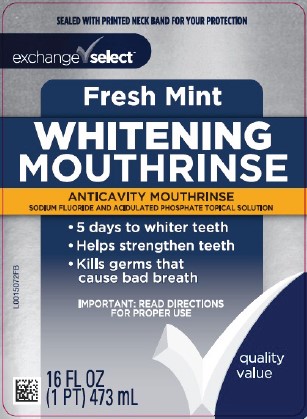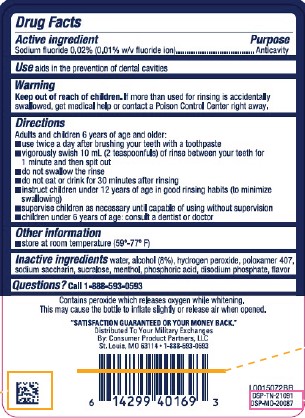 DRUG LABEL: Anticavity
NDC: 55301-435 | Form: MOUTHWASH
Manufacturer: Your Military Exchanges
Category: otc | Type: HUMAN OTC DRUG LABEL
Date: 20260212

ACTIVE INGREDIENTS: SODIUM FLUORIDE 0.1 mg/1 mL
INACTIVE INGREDIENTS: ALCOHOL; WATER; HYDROGEN PEROXIDE; POLOXAMER 407; SACCHARIN SODIUM; SUCRALOSE; MENTHOL; PHOSPHORIC ACID; SODIUM PHOSPHATE, DIBASIC, ANHYDROUS

Exchange Select 435.000/435AA
Glowing White Anticavity Mouthrinse

Active Ingredient

Sodium fluoride 0.02% (0.01% w/v fluoride ion)

Purpose

Anticavity

Use

Aids in the prevention of dental cavities

Warnings

For this product

Keep out of reach of children.

If more than used for rinsing is accidentally swallowed, get medical help or contact a Poison Control Center right away.

Directions

Adults and children 6 years of age and older:

- use twice a day after brushing your teeth with a toothpaste
- vigorously swish 10 mL (2 teaspoonfuls) of rinse between your teeth for 1 minute and then spit out
- do not swallow the rinse
- do not eat or drink for 30 minutes after rinsing
- instruct children under 12 years of age in good rinsing habits (to minimize swallowing)
- supervise children as necessary until capable of using without supervision
- children under 6 years of age: consult a dentist or doctor

Other information

- store at room temperature (59º-77ºF)

Inactive ingredients

water, alcohol (8%), hydrogen peroxide, poloxamer 407, sodium saccharin, sucralose, menthol, phosphoric acid, disodium phosphate, flavor

Questions?

Call 1-888-593-0593

Disclaimer

Contains peroxide which releases oxygen while whitening.

This may cause the bottle to inflate slightly or release air when opened.

ADVERSE REACTION

"Satisfaction guaranteed or your money back."

Distributed To Your Military Exchanges

By: Consumer Product Partners, LLC

St. Louis, MO 63114

1-888-593-0593

DSP-TN-21091

DSP-MO-20087

Principal display panel

SEALED WITH PRINTED NECK BAND FOR YOUR PROTECTION

Exchange Select™

Fresh Mint

WHITENING

MOUTHRINSE

ANTICAVITY MOUTHRINSE

SODIUM FLUORIDE AND ACIDULATED PHOSPHATE TOPICAL SOLUTION

- 5 days to whiter teeth
- Helps strengthen teeth
- Kills germs that cause bad breath

IMPORTANT: READ DIRECTIONS FOR PROPER USE

quality value

16 FL OZ (1 PT) 474 mL